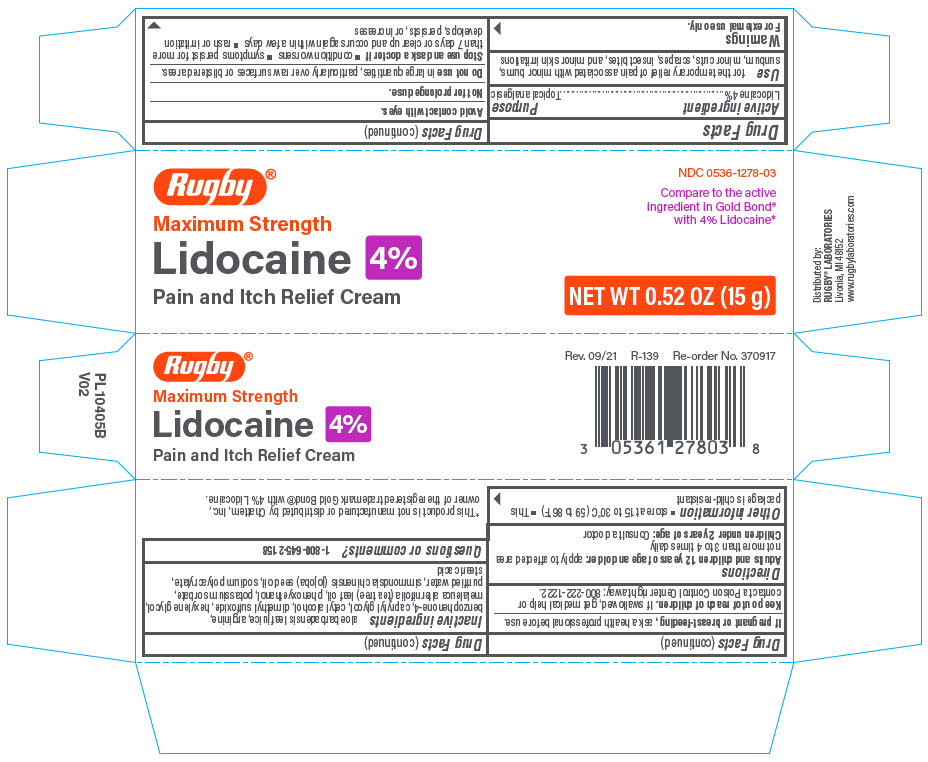 DRUG LABEL: RUGBY LIDOCAINE
NDC: 0536-1278 | Form: CREAM
Manufacturer: Rugby Laboratories
Category: otc | Type: HUMAN OTC DRUG LABEL
Date: 20250916

ACTIVE INGREDIENTS: LIDOCAINE 40 mg/1 g
INACTIVE INGREDIENTS: ALOE VERA LEAF; ARGININE; SULISOBENZONE; CETYL ALCOHOL; DIMETHYL SULFOXIDE; ANGOPHORA COSTATA WHOLE; MELALEUCA ALTERNIFOLIA LEAF; WATER; JOJOBA OIL; SODIUM POLYACRYLATE (2500000 MW); STEARIC ACID; CAPRYLYL GLYCOL

RUGBY® LIDOCAINE 4%

Drug Facts

Active ingredient

Lidocaine 4%

Purpose

Topical analgesic

Use

for the temporary relief of pain associated with minor burns, sunburn, minor cuts, scrapes, insect bites, and minor skin irritations

Warnings

For external use only.

Avoid contact with eyes.

Not for prolonged use.

Do not use in large quantities, particularly over raw surfaces or blistered areas.

Stop use and ask a doctor if

- condition worsens
- symptoms persist for more than 7 days or clear up and occurs again within a few days
- rash or irritation develops, persists, or increases

PREGNANCY OR BREAST FEEDING

If pregnant or breast-feeding, ask a health professional before use.

Keep out of reach of children. If swallowed, get medical help or contact a Poison Control Center right away: 800-222-1222.

Directions

Adults and children 12 years of age and older: apply to affected area not more than 3 to 4 times daily

Children under 2 years of age: Consult a doctor

Other information

- store at 15 to 30°C (59 to 86°F)
- This package is child-resistant

Inactive ingredients

aloe barbadensis leaf juice, arginine, benzophenone-4, caprylyl glycol, cetyl alcohol, dimethyl sulfoxide, hexylene glycol, melaleuca alternifolia (tea tree) leaf oil, phenoxyethanol, potassium sorbate, purified water, simmondsia chinensis (jojoba) seed oil, sodium polyacrylate, stearic acid

Questions or comments?

1-800-645-2158

Distributed by:
RUGBY® LABORATORIES
Livonia, MI 48152

PRINCIPAL DISPLAY PANEL - 15 g Tube Carton

Rugby®

Maximum Strength
Lidocaine 4%
Pain and Itch Relief Cream

NDC 0536-1278-03

Compare to the active
ingredient in Gold Bond®
with 4% Lidocaine*

NET WT 0.52 OZ (15 g)